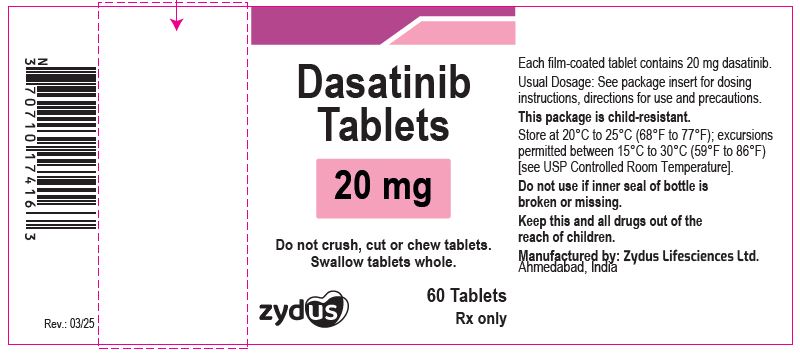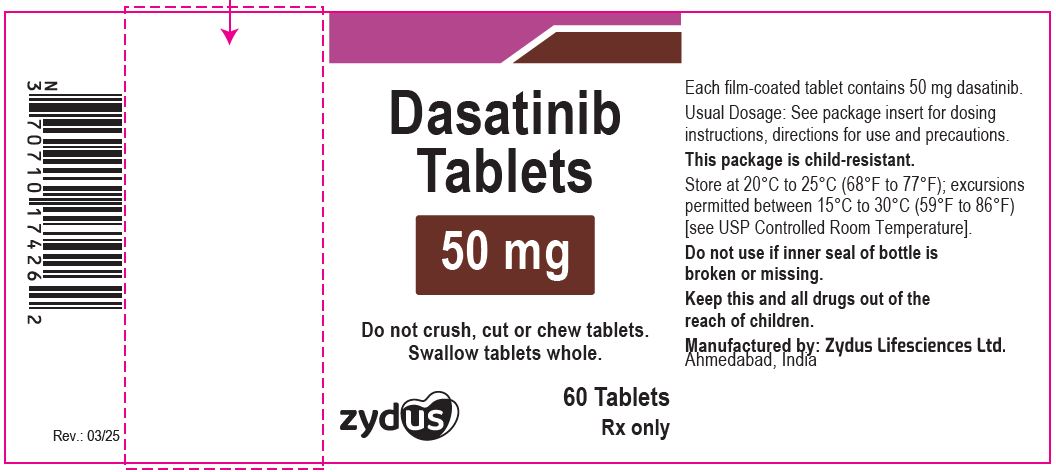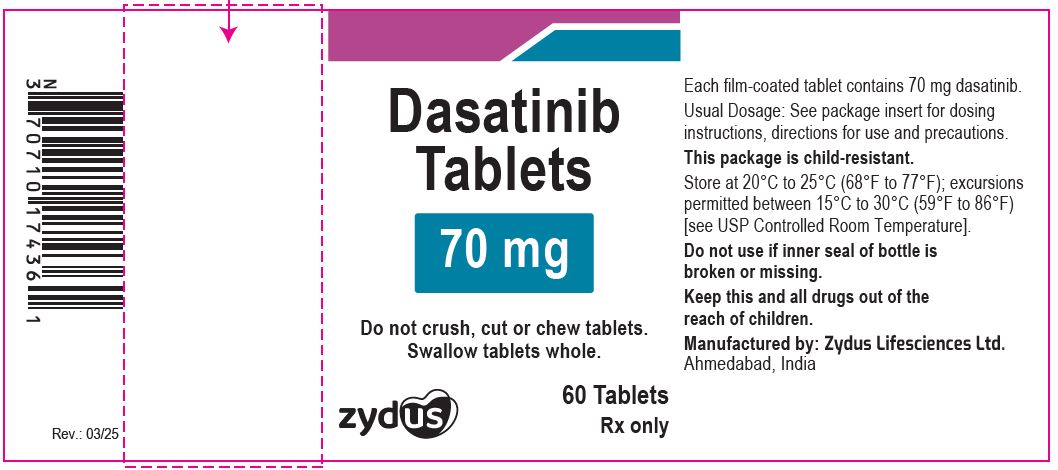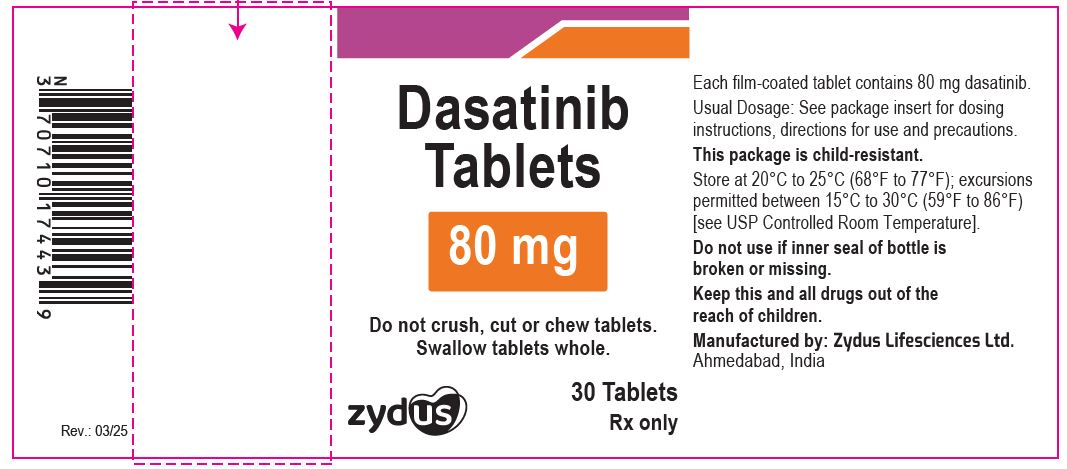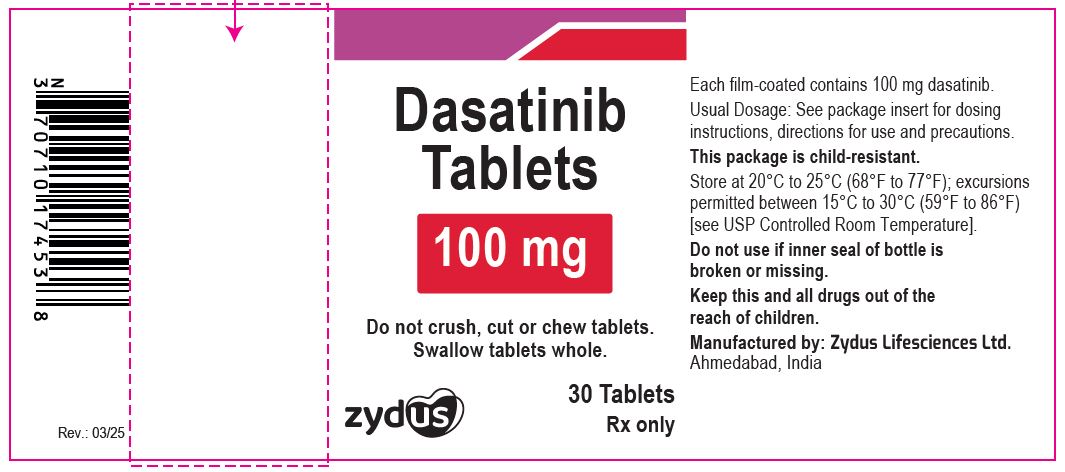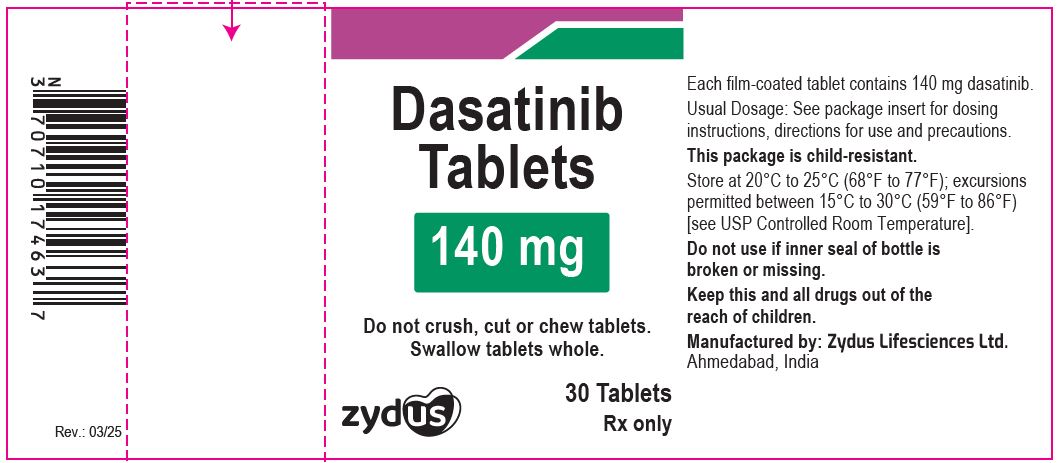 DRUG LABEL: dasatinib
NDC: 70771-1901 | Form: TABLET
Manufacturer: Zydus Lifesciences Limited
Category: prescription | Type: HUMAN PRESCRIPTION DRUG LABEL
Date: 20250304

ACTIVE INGREDIENTS: DASATINIB 20 mg/1 1
INACTIVE INGREDIENTS: CROSCARMELLOSE SODIUM; GLYCERYL MONO- AND DICAPRYLOCAPRATE; HYDROXYPROPYL CELLULOSE, UNSPECIFIED; LACTOSE MONOHYDRATE; MAGNESIUM STEARATE; MICROCRYSTALLINE CELLULOSE 101; POLYVINYL ALCOHOL, UNSPECIFIED; SILICON DIOXIDE; SODIUM LAURYL SULFATE; TALC; TITANIUM DIOXIDE

Dasatinib Tablets for Oral Use

PACKAGE LABEL.PRINCIPAL DISPLAY PANEL

NDC 70771-1901-6

Dasatinib Tablets, 20 mg

60 Tablets

Rx only

Zydus

NDC 70771-1902-6

Dasatinib Tablets, 50 mg

60 Tablets

Rx only

Zydus

NDC 70771-1903-6

Dasatinib Tablets, 70 mg

60 Tablets

Rx only

Zydus

NDC 70771-1904-3

Dasatinib Tablets, 80 mg

30 Tablets

Rx only

Zydus

NDC 70771-1905-3

Dasatinib Tablets, 100 mg

30 Tablets

Rx only

Zydus

NDC 70771-1906-3

Dasatinib Tablets, 140 mg

30 Tablets

Rx only

Zydus